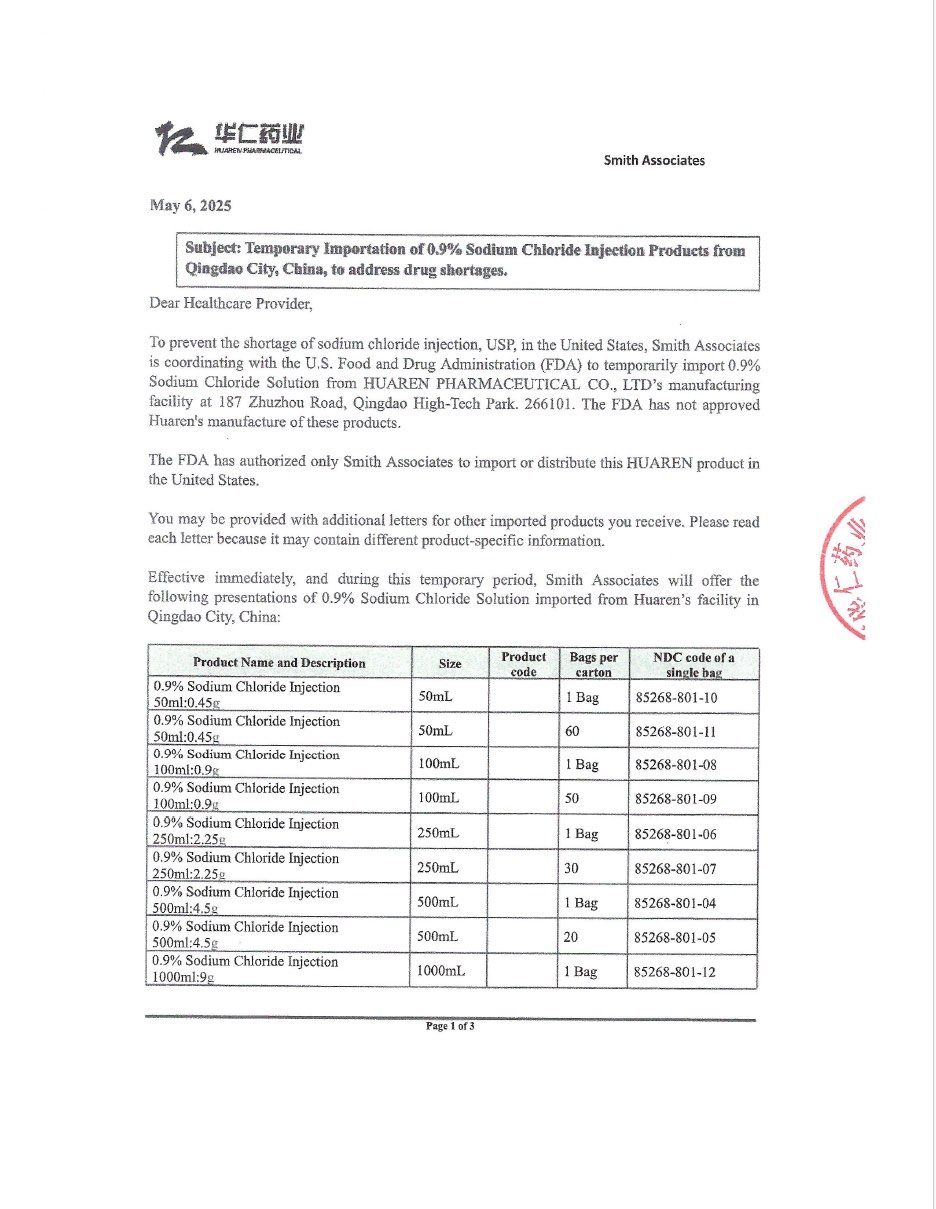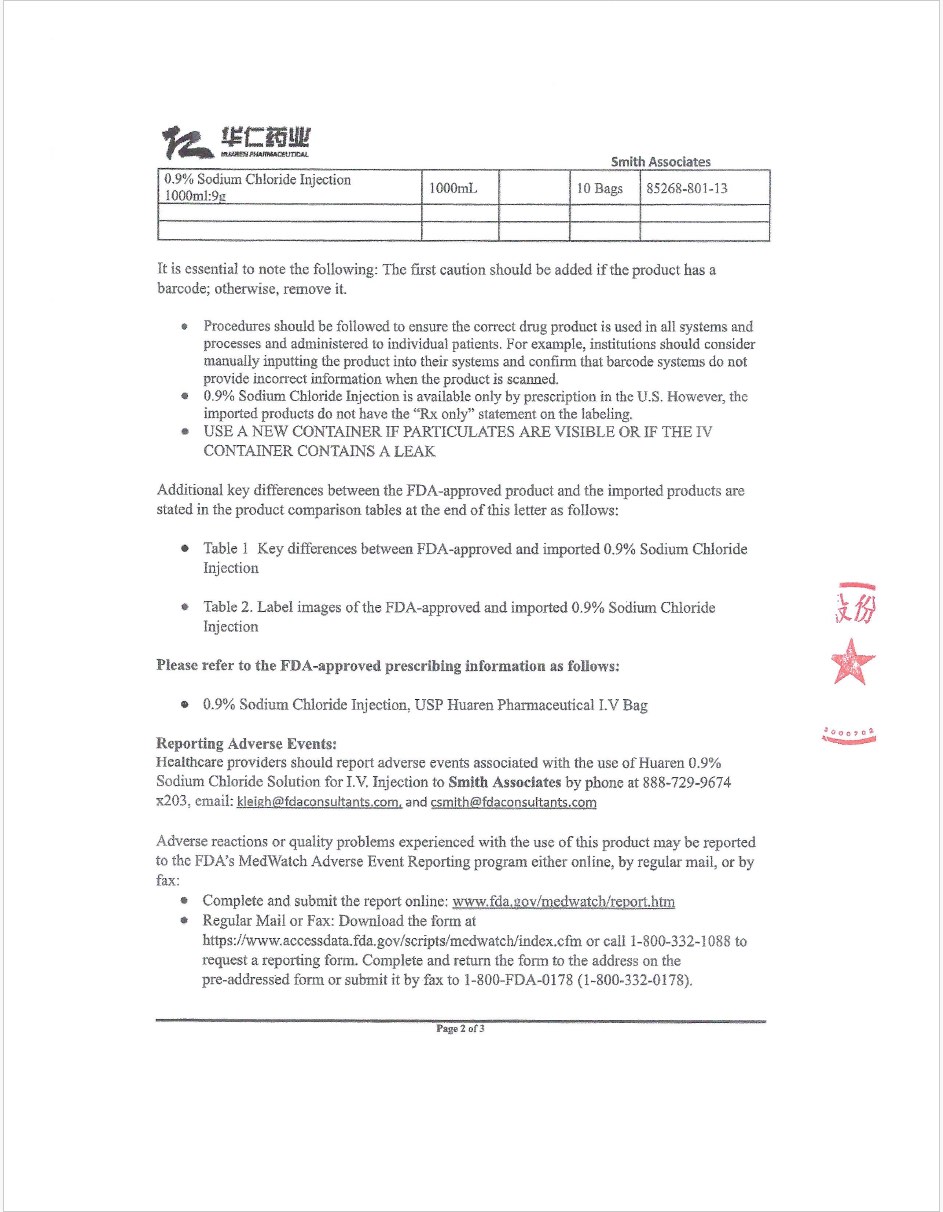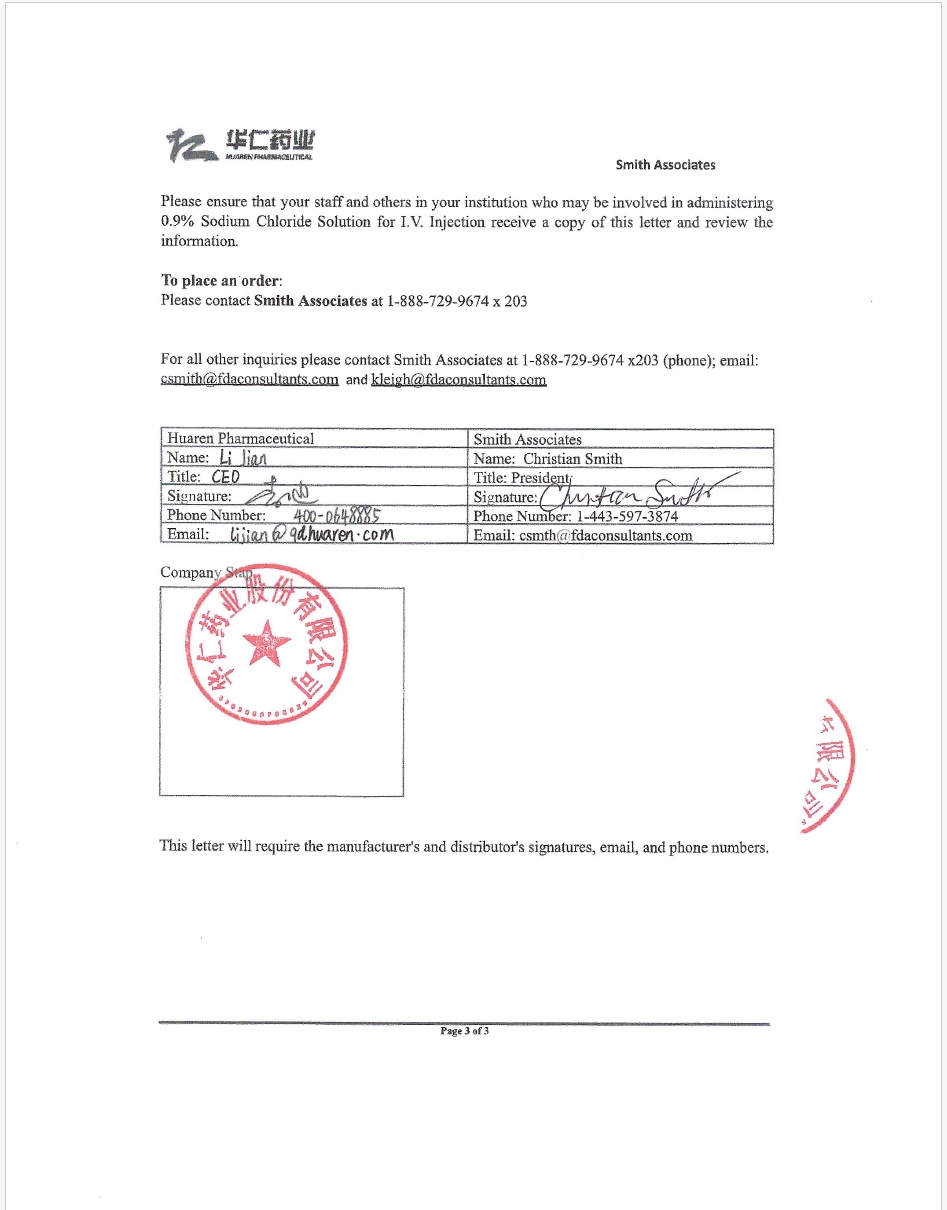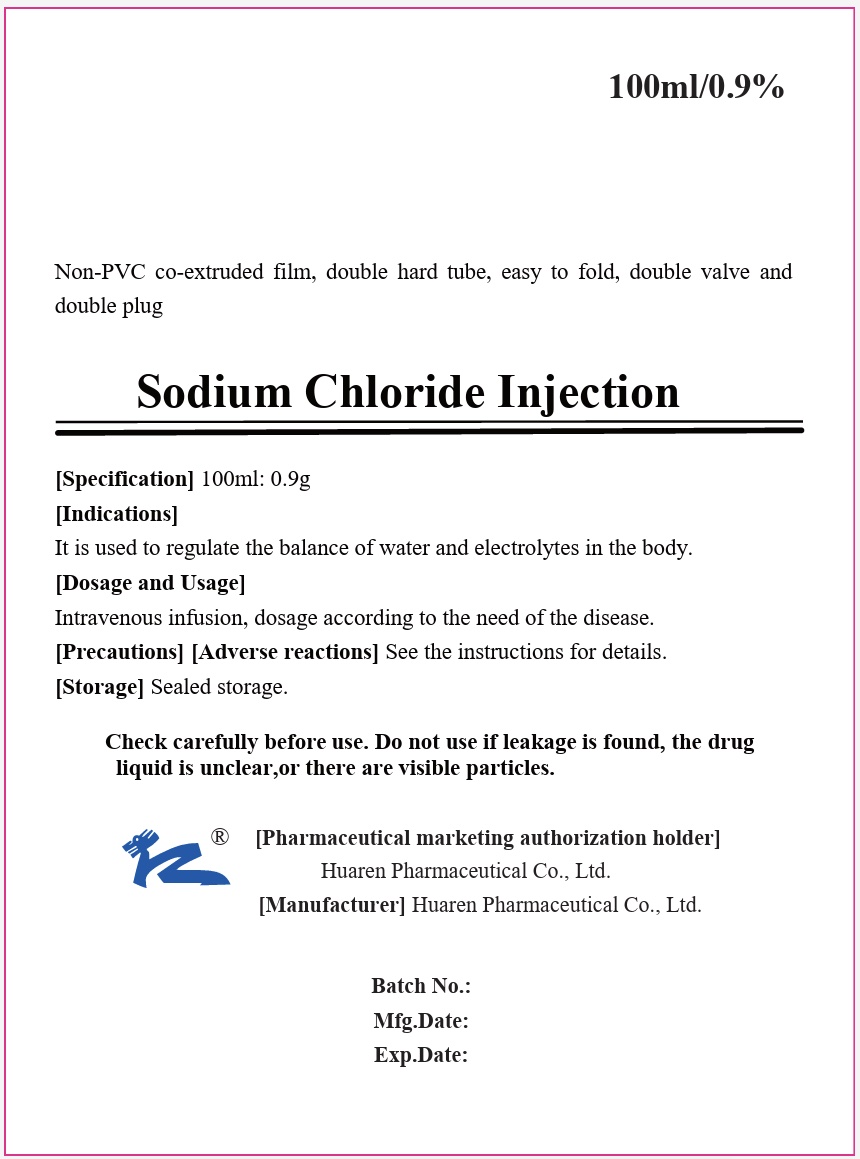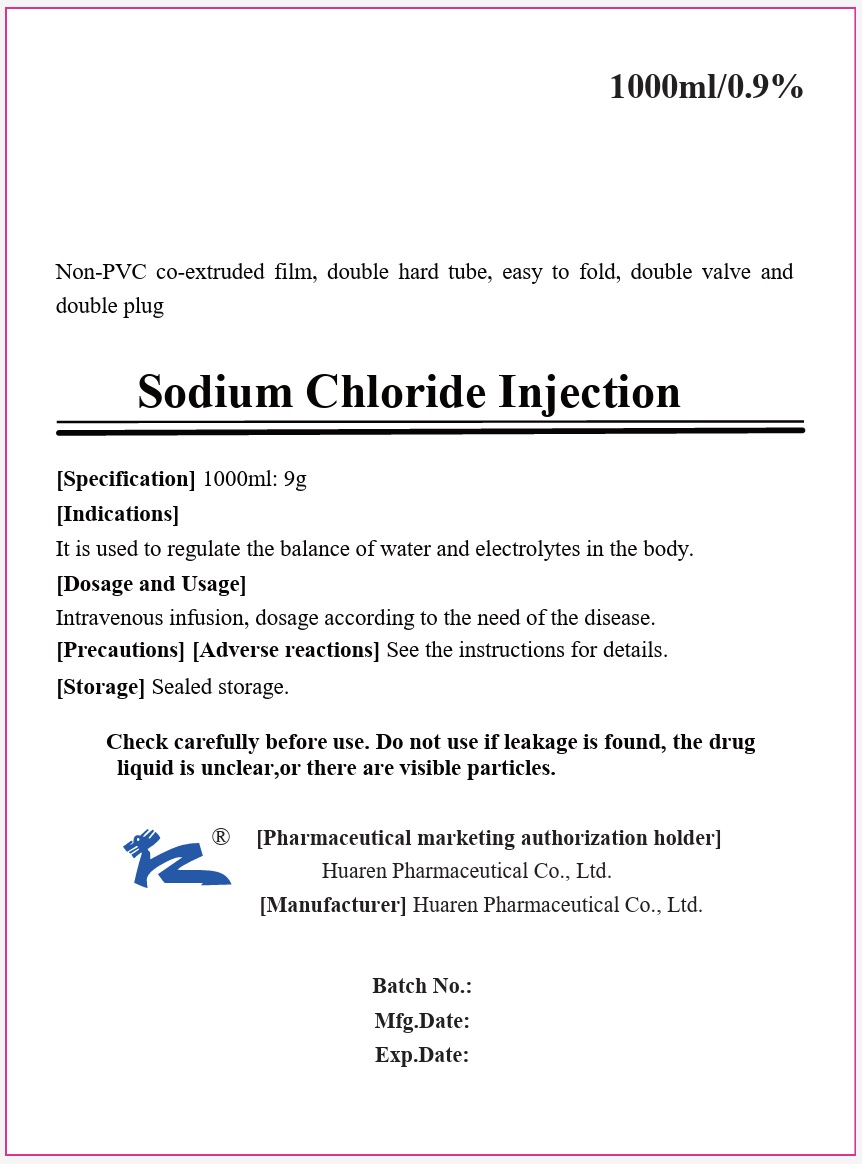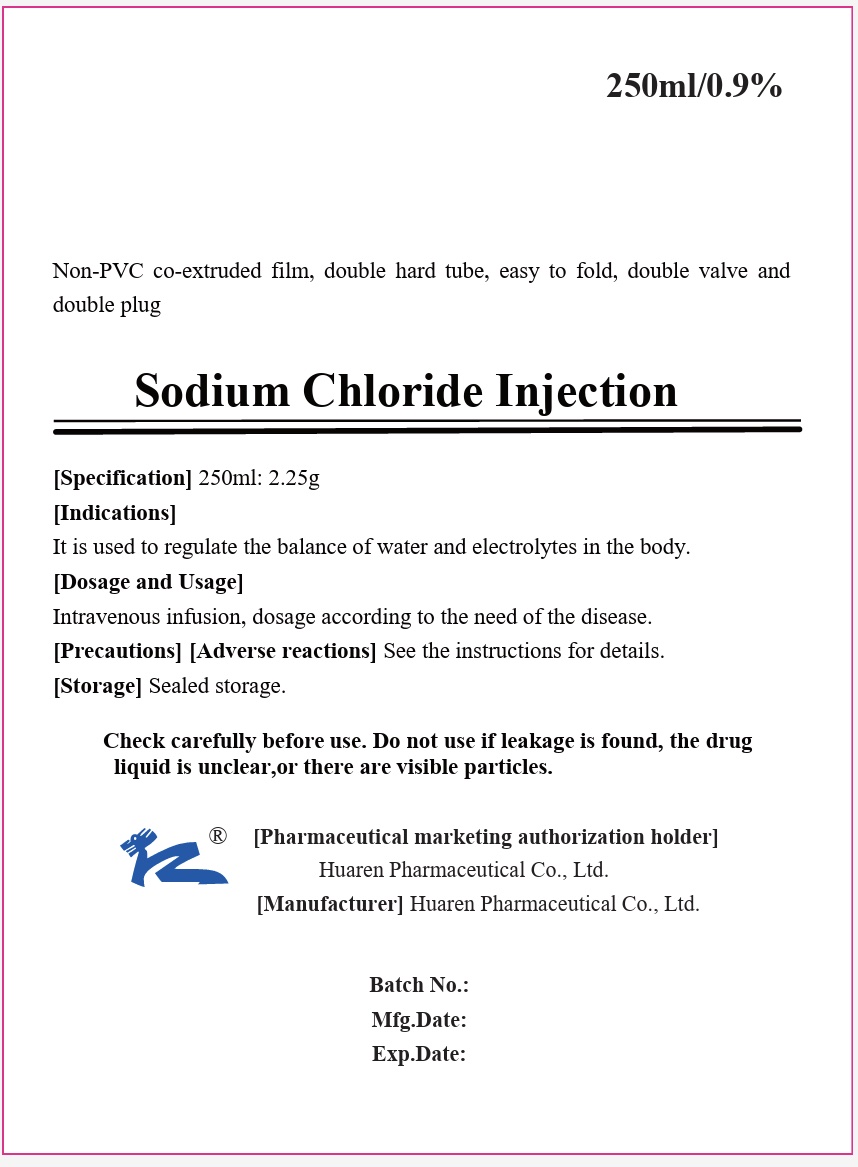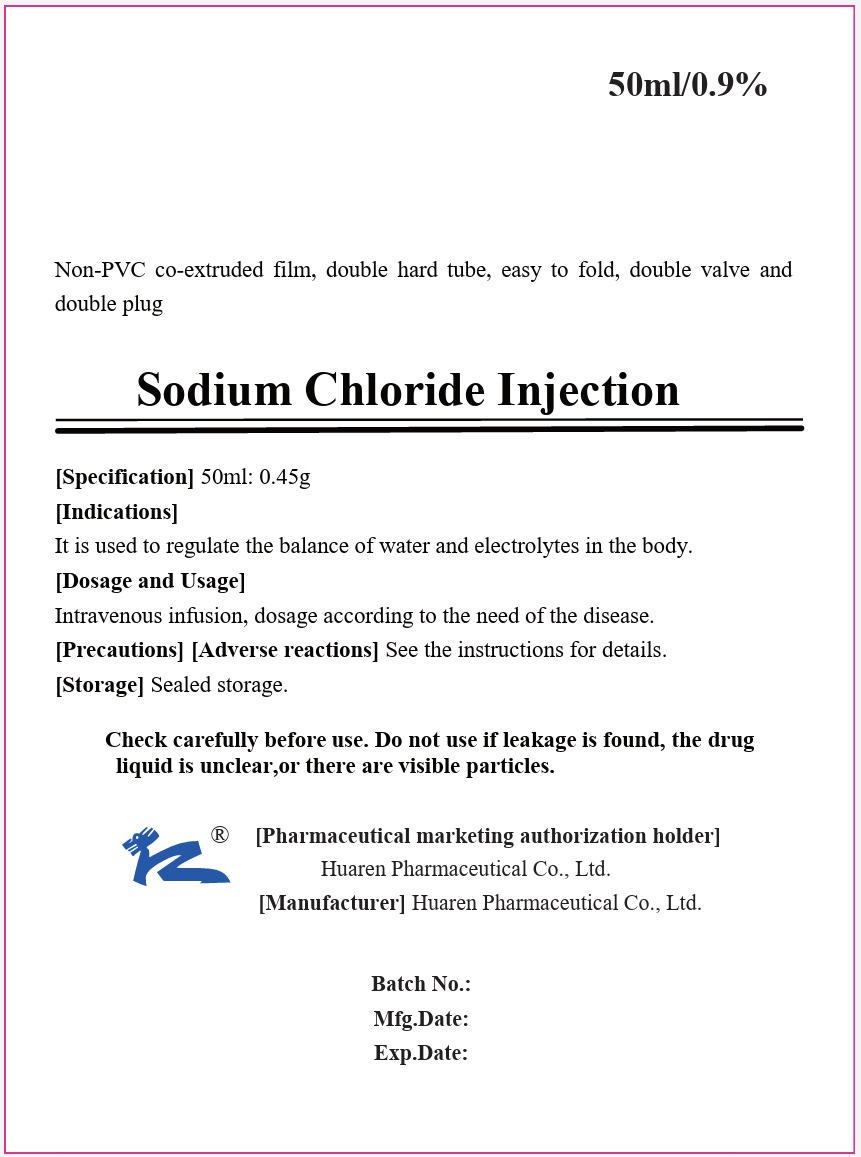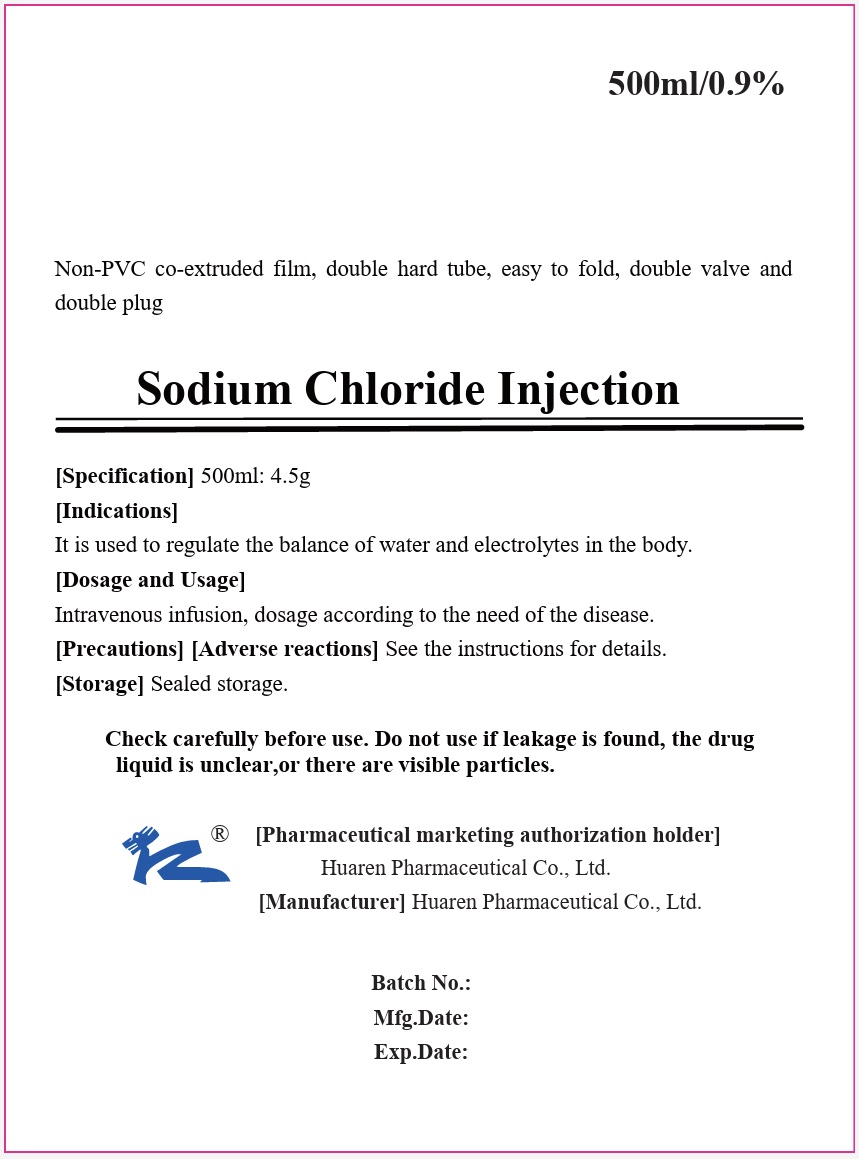 DRUG LABEL: SODIUM CHLORIDE 0.9%
NDC: 85268-806 | Form: INJECTION, SOLUTION
Manufacturer: Huaren Pharmaceutical Co., Ltd.
Category: prescription | Type: HUMAN PRESCRIPTION DRUG LABEL
Date: 20250602

ACTIVE INGREDIENTS: SODIUM CHLORIDE 0.9 g/100 mL
INACTIVE INGREDIENTS: WATER

0.9% Sodium Chloride - Q (EUA)

SODIUM CHLORIDE INJECTION, USP BAG

Sodium Chloride Injection Instructions

Please read the instructions carefully and use under the guidance of a physician.

Check carefully before use. Do not use if leakage is found, the drug liquid is unclear, or there are visible particles, do not use.

INGREDIENTS

This product is an isotonic sterilizing aqueous solution of sodium chloride.

Chemical Name : Sodium chloride

Molecular Formula: NaCl

Molecular Weight: 58.44

Osmolality: 260~320 mOsmol/kg.

CHARACTER

This product is a colorless and clear liquid.

INDICATIONS

It is used to regulate the balance of water and electrolytes in the body.

SPECIFICATION

50ml: 0.45g; 100ml: 0.9g; 250ml: 2.25g; 500ml: 4.5g; 1000ml: 9g

DOSAGE AND USAGE

Intravenous infusion, dosage according to the need of the disease.

ADVERSE REACTIONS

Excessive and rapid infusion can cause water and sodium retention, edema, elevated blood pressure, rapid heart rate, chest tightness, dyspnea, and even acute left heart failure.

PRECAUTIONS

Use with caution in the following cases:

1. Edematous diseases, such as nephrotic syndrome, cirrhosis, ascites, congestive heart failure, acute left heart failure, brain edema, and idiopathic edema
2. Acute renal failure, oliguria stage, chronic renal failure, urine volume decreased, and poor response to diuretic drugs;
3. Hypertension;
4. Hypokalemia.

Follow-up examination:

1. Serum sodium, potassium, chlorine concentration;
2. Blood acid-base balance index;
3. Kidney function;
4. Blood pressure and cardiopulmonary function.

MEDICATION IN PREGNANT WOMEN AND LACTATING WOMEN

Not clear.

MEDICATION IN CHILDREN

The amount and speed of fluid supplementation should be strictly controlled.

MEDICATION IN THE ELDERLY

The amount and speed of fluid supplementation should be strictly controlled.

DRUG INTERACTIONS

Should not be used with drugs with known incompatibility contraindications.

DRUG OVERDOSE

For those with existing acidosis, a large amount of this product can cause hyperchloric acidosis.

PHARMACOLOGY AND TOXICOLOGY

Sodium and chlorine are important electrolytes in the body, mainly in the extracellular fluid, and play a very important role in maintaining the normal blood and extracellular fluid volume and osmotic pressure of the human body. The normal serum sodium concentration is 135~145mmol/L, accounting for 92% of the plasma cation and 90% of the total osmotic pressure, so the amount of plasma sodium plays a decisive role in the osmotic pressure. The normal serum chlorine concentration is 98~106mmol/L, which is mainly regulated by the human body through the hypothalamus, posterior pituitary and kidney to maintain the stability of body fluid volume and osmotic pressure.

PHARMACOKINETICS

In the gastrointestinal tract, sodium is absorbed almost entirely through the active transport of intestinal mucosal cells. Sodium is excreted primarily by the kidneys.

STORAGE

Sealed storage.

PACKAGE

1. Plastic infusion bag (non-PVC co-extruded film, double hard tube, easy to fold, double valve and double plug). 50ml/ bag, 100ml/ bag, 250ml/ bag, 500ml/ bag, 10O0ml/ bag.
2. Plastic infusion bag (non-PVC co-extruded film, double hard tube, easy to fold, double valve double plug, double aseptic packaging). 50ml/ bag, 100ml/ bag, 250ml/ bag, 500ml/ bag, 1000ml/ bag.

VALIDITY

1. The product of 50ml,100ml, and 1000ml specifications is valid for 24 months.
2. The validity period of 250ml,500ml is 36 months.

OTHER INFORMATION

[EXECUTIVE STANDARD]

Pharmacopoeia of the People's Republic of China (2020, Volume II)

[APPROVAL NUMBER]

GuoYaoZhunZi: H20033208 (50ml: 0.45g)

GuoYaoZhunZi: H20023682 (100ml: 0.9g)

GuoYaoZhunZi: H20023146 (250ml: 2.25g)

GuoYaoZhunZi: H20023145 (500ml: 4.5g)

GuoYaoZhunZi: H20023750 (1000ml: 9g)

[PHARMACEUTICAL MARKETING AUTHORIZATION HOLDER]

Name: Huaren Pharmaceutical Co., Ltd.

Registered Address: No. 187, Zhuzhou Road, Qingdao High-tech Park, China.

[MANUFACTURER]

Enterprise Name: Huaren Pharmaceutical Co., Ltd.

Production Address: No. 187, Zhuzhou Road, Qingdao High-tech Park, China. Zip code: 266101

Tel.: 400-0648885 0532-67709071

Fax: 0532-88702625

Website: http//www.qdhuaren.com